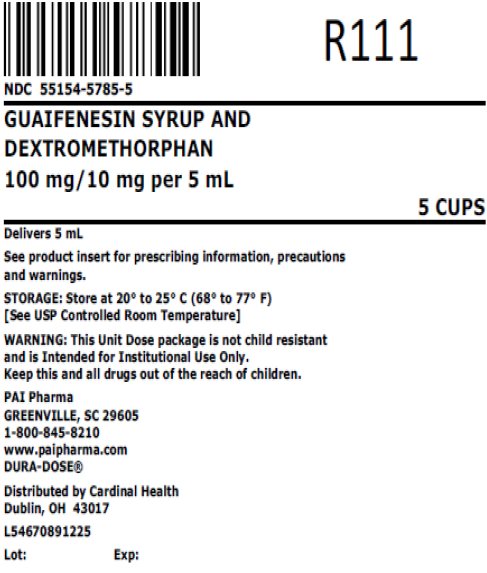 DRUG LABEL: GUAIFENESIN DM
NDC: 55154-5785 | Form: SYRUP
Manufacturer: Cardinal Health 107, LLC
Category: otc | Type: HUMAN OTC DRUG LABEL
Date: 20251218

ACTIVE INGREDIENTS: GUAIFENESIN 100 mg/5 mL; DEXTROMETHORPHAN 10 mg/5 mL
INACTIVE INGREDIENTS: ANHYDROUS CITRIC ACID; FD&C RED NO. 40; GLYCERIN; MENTHOL, UNSPECIFIED FORM; WATER; SODIUM BENZOATE; SODIUM CITRATE, UNSPECIFIED FORM; SACCHARIN SODIUM; SUCROSE

GUAIFENESIN DM

PURPOSE

Non-Narcotic, Alcohol Free
Expectorant/Cough Suppressant

DESCRIPTION

Each 5 mL (1 teaspoonful) contains:
Guaifenesin | 100 mg
Dextromethorphan Hydrobromide | 10 mg

INACTIVE INGREDIENT

Inactive Ingredients: Citric acid, FD&C Red No. 40, flavoring, glycerin, menthol, purified water, sodium benzoate, sodium citrate, sodium saccharin, and sucrose.

Sodium Content: 4 mg/5 mL

USES

- helps loosen phlegm (mucus) and thin bronchial secretions to make coughs more productive
- temporarily relieves cough due to minor throat and bronchial irritation as may occur with a cold

WARNINGS

Do not use if you are now taking a prescription monoamine oxidase inhibitor (MAOI) (certain drugs for depression, psychiatric, or emotional conditions, or Parkinson's disease), or for 2 weeks after stopping the MAOI drug. If you do not know if your prescription drug contains an MAOI, ask a doctor or pharmacist before taking this product.

Ask a doctor before use if you have

- cough that occurs with too much phlegm (mucus)
- cough that lasts or is chronic such as occurs with smoking, asthma, chronic bronchitis, or emphysema

Stop use and ask a doctor if

- cough lasts more than 7 days, comes back, or is accompanied by fever, rash, or persistent headache. These could be signs of a serious condition.
- you are hypersensitive to any of the ingredients.

PREGNANCY OR BREAST FEEDING

If pregnant or breast-feeding, ask a health professional before use.

Keep out of reach of children. In case of overdose, get medical help or contact a Poison Control Center right away.

Professional Note: Guaifenesin has been shown to produce a color interference with certain clinical laboratory determinations of 5-hydroxyindoleacetic acid (5-HIAA) and vanillylmandelic acid (VMA).

DOSAGE AND ADMINISTRATION

DIRECTIONS: Follow dosage below or use as directed by a physician.

- do not take more than 6 doses in any 24-hour period.

age | dose
adults and children 12 years and over | 10 mL (2 teaspoonfuls) every 4 hours
children 6 years to under 12 years | 5 mL (1 teaspoonful) every 4 hours
children 2 years to under 6 years | 2.5 mL (1/2 teaspoonful) every 4 hours
children under 2 years | ask a doctor

HOW SUPPLIED: Guaifenesin Syrup and Dextromethorphan is a red, cherry flavored syrup supplied in the following oral dosage forms:

Overbagged with 5 x 5 mL unit dose cups in each bag, NDC 55154-5785-5

WARNING: This Unit Dose package is not child resistant and is Intended for Institutional Use Only. Keep this and all drugs out of the reach of children.

STORAGE AND HANDLING

STORAGE: Keep tightly closed. Store at controlled room temperature, 20°-25°C (68°-77°F) [See USP]. Protect from light.

MANUFACTURED BY

Pharmaceutical Associates, Inc.
Greenville, SC 29605
www.paipharma.com

Distributed By:

Cardinal Health

Dublin, OH 43017

L54670891225

R11/16

Principal Display Panel

NDC 55154-5785-5

GUAIFENESIN SYRUP AND

DEXTROMETHORPHAN

100 mg/10 mg per 5 mL

5 CUPS